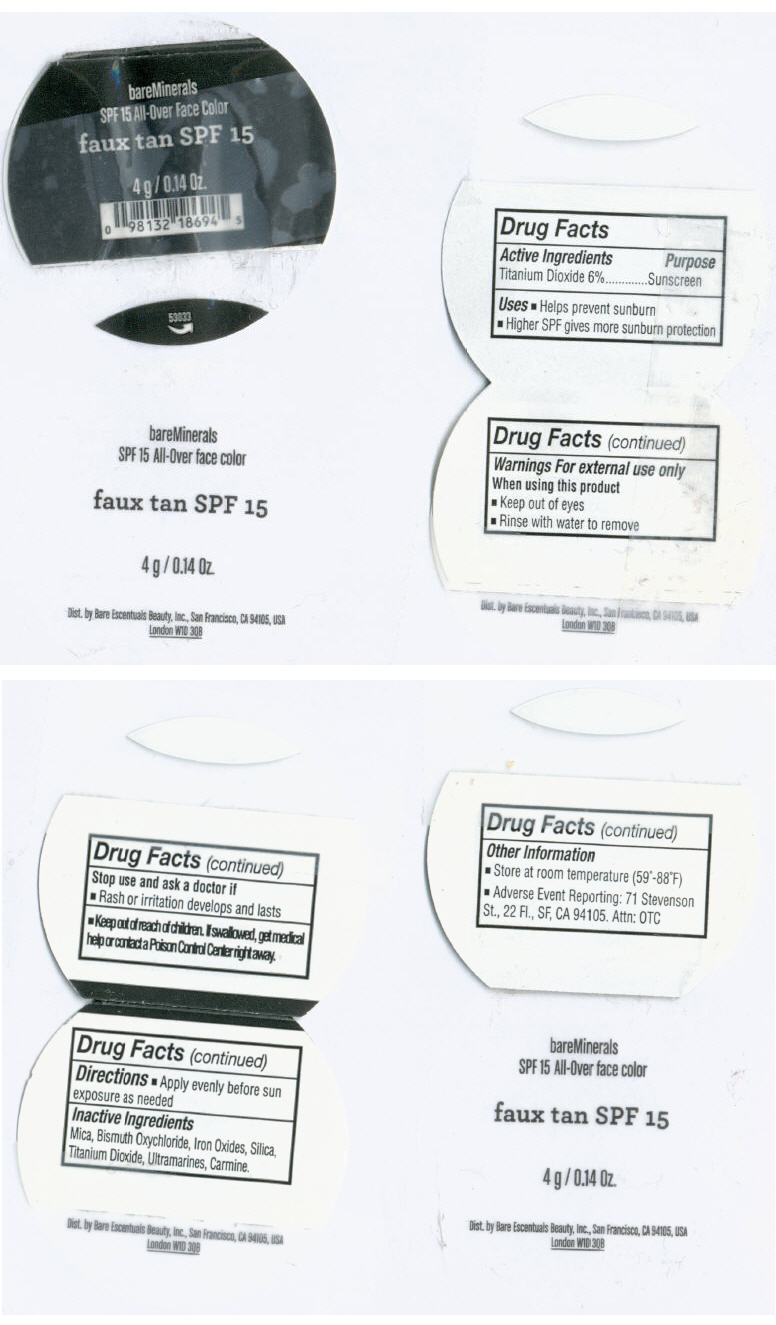 DRUG LABEL: BareMinerals Faux Tan
NDC: 98132-158 | Form: POWDER
Manufacturer: Bare Escentuals Beauty Inc.
Category: otc | Type: HUMAN OTC DRUG LABEL
Date: 20110726

ACTIVE INGREDIENTS: Titanium Dioxide 25 g/100 g
INACTIVE INGREDIENTS: Mica; Bismuth Oxychloride; FERRIC OXIDE RED; Silicon Dioxide; Ultramarine Blue; Cochineal

bareMinerals
SPF 15 All-Over Face Color

Drug Facts

Active Ingredients

Titanium Dioxide 6%

Purpose

Sunscreen

Uses

- Helps prevent sunburn
- Higher SPF gives more sunburn protection

Warnings

For external use only

When using this product

- Keep out of eyes
- Rinse with water to remove

Stop use and ask a doctor if

- Rash or irritation develops and lasts

- Keep out of reach of children. If swallowed, get medical help or contact a Poison Control Center right away.

Directions

- Apply evenly before sun exposure as needed

Inactive Ingredients

Mica, Bismuth Oxychloride, Iron Oxides, Silica, Titanium Dioxide, Ultramarines, Carmine.

Other Information

- Store at room temperature (59°-88°F)
- Adverse Event Reporting: 71 Stevenson St., 22 Fl., SF, CA 94105. Attn: OTC

Dist. by Bare Escentuals Beauty, Inc., San Francisco, CA 94105, USA

PRINCIPAL DISPLAY PANEL - 4 g Jar Label

bareMinerals
SPF 15 All-Over Face Color

faux tan SPF 15

4 g / 0.14 Oz.